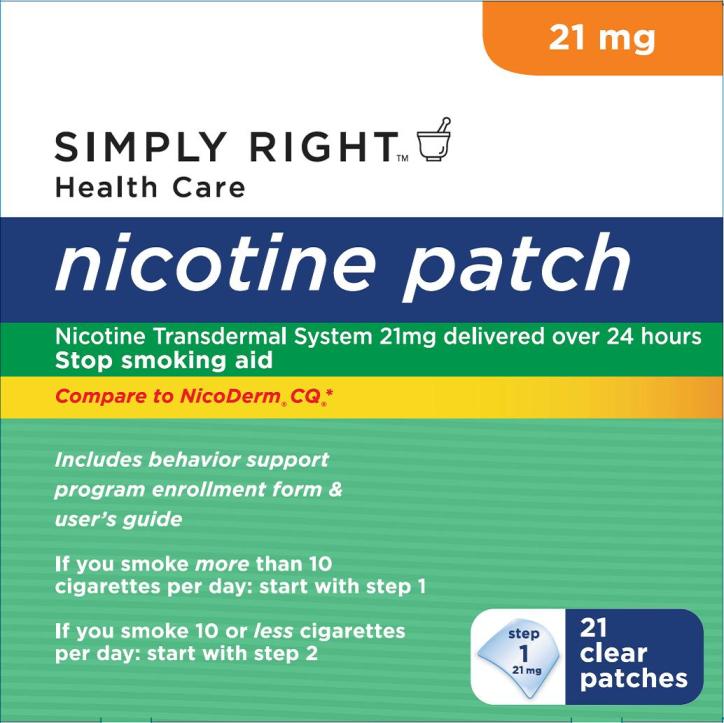 DRUG LABEL: Nicotine
NDC: 68196-194 | Form: PATCH, EXTENDED RELEASE
Manufacturer: Sam's West Inc
Category: otc | Type: HUMAN OTC DRUG LABEL
Date: 20250610

ACTIVE INGREDIENTS: NICOTINE 21 mg/24 h
INACTIVE INGREDIENTS: ETHYLENE-VINYL ACETATE COPOLYMER (40% VINYL ACETATE); HIGH DENSITY POLYETHYLENE

Drug Facts

Active ingredient (in each patch)

Nicotine, 21 mg delivered over 24 hours

Purpose

Stop smoking aid

Use

reduces withdrawal symptoms, including nicotine craving, associated with quitting smoking

Warnings

If you are pregnant or breast-feeding, only use this medicine on the advice of your health care provider.

Smoking can seriously harm your child. Try to stop smoking without using any nicotine replacement medicine. This medicine is believed to be safer than smoking. However, the risks to your child from this medicine are not fully known.

Do Not Use

- if you continue to smoke, chew tobacco, use snuff, or use a nicotine gum or other nicotine containing products

Ask a doctor before use if you have

- heart disease, recent heart attack, or irregular heartbeat. Nicotine can increase your heart rate.
- high blood pressure not controlled with medication. Nicotine can increase your blood pressure.
- an allergy to adhesive tape or have skin problems because you are more likely to get rashes.

Ask a doctor or pharmacist before use if you are

- using a non-nicotine stop smoking drug
- taking a prescription medicine for depression or asthma. Your prescription dose may need to be adjusted.

When using this product

- do not smoke even when not wearing the patch. The nicotine in your skin will still be entering your blood stream for several hours after you take off the patch.
- if you have vivid dreams or other sleep disturbances remove this patch at bedtime

Stop use and ask a doctor if

- skin redness caused by the patch does not go away after four days, or if your skin swells, or you get a rash
- irregular heartbeat or palpitations occur
- you get symptoms of nicotine overdose such as nausea, vomiting, dizziness, weakness and rapid heartbeat

Keep out of reach of children and pets.

Used patches have enough nicotine to poison children and pets. If swallowed, get medical help or contact a Poison Control Center right away. Dispose of the used patches by folding sticky ends together. Replace in pouch and discard.

Directions

- if you are under 18 years of age, ask a doctor before use
- before using this product, read the enclosed User’s Guide for complete directions and other information
- stop smoking completely when you begin using the patch
- if you smoke more than 10 cigarettes per day, use according to the following 10 week schedule:

STEP 1 | STEP 2 | STEP 3
Use one 21 mg patch/day | Use one 14 mg patch/day | Use one 7 mg patch/day
Weeks 1-6 | Weeks 7-8 | Weeks 9-10

- if you smoke 10 or less cigarettes per day, do not use STEP 1 (21mg). Start with STEP 2 (14mg), for 6 weeks, then STEP 3 (7mg) for 2 weeks and then stop.
- steps 2 and 3 allow you to gradually reduce your level of nicotine. Completing the full program will increase your chances of quitting successfully.
- apply one new patch every 24 hours on skin that is dry, clean and hairless. Save pouch for disposing of the patch after use.
- remove backing from patch and immediately press onto skin. Hold for 10 seconds.
- wash hands after applying or removing patch. Throw away the patch by folding sticky ends together. Replace in its pouch and discard. See enclosed User’s Guide for safety and handling.
- you may wear the patch for 16 or 24 hours
- if you crave cigarettes when you wake up, wear the patch for 24 hours
- if you have vivid dreams or other sleep disturbances, you may remove the patch at bedtime and apply a new one in the morning
- the used patch should be removed and a new one applied to a different skin site at the same time each day
- do not wear more than one patch at a time
- do not cut patch in half or into smaller pieces
- do not leave patch on for more than 24 hours because it may irritate your skin and loses strength after 24 hours
- stop using the patch at the end of 10 weeks. If you started with STEP 2, stop using the patch at the end of 8 weeks. If you still feel the need to use the patch, talk to your doctor.

Other information

store at 20-25°C (68-77°F)

Inactive ingredients

ethylene vinyl acetate-copolymer, polyisobutylene and high density polyethylene between clear polyester backings

Questions or comments?

call toll-free 1-866-255-5205 (English/Spanish) weekdays

TO INCREASE YOUR SUCCESS IN QUITTING:

- You must be motivated to quit.
- Complete the full treatment program, applying a new patch every day.
- Use with a support program as described in the enclosed User’s Guide.
For your family’s protection, Nicotine Patches are supplied in child-resistant pouches. Do not use if individual pouch/packet is damaged or open.
Nicotine transdermal system 21 mg delivered over 24 hours
Stop smoking aid
- Not for sale to those under 18 years of age.
- Prrof of age required.
- Not for sale in vending machines or from any source where proof of age cannot be verified.
Free Audio CD upon request. See inside.
What is the Nicotine Patch and How is it Used?
Nicotine Patch is a small, nicotine-containing patch. When you put on a Nicotine Patch, nicotine passes through the skin and into your body. Nicotine Patch is very thin and uses special material to control how fast nicotine passes through the skin. Unlike the sudden jolts of nicotine delivered by cigarettes, the amount of nicotine you receive remains relatively smooth throughout the 24 or 16-hour period you wear the Nicotine Patch. This helps to reduce cravings you may have for nicotine.
Read carton and enclosed User’s Guide before using this product. Keep the carton and User’s Guide. They contain important information.
THE SIMPLY RIGHT™ PROMISE
Simply Right is dedicated to providing healthful, gentle, and safe personal care products for the entire family. We continuously strive to be your trusted partner in wellness and exceed your expectations.
We would like to hear from you with any comments or suggestions. In the continental US or Canada, you can call us toll-free at 1-800-255-5205, Monday through Friday, from 8 am to 5 pm CST. Or you can send us an email at samsclub.com.
Distributed by:
SAM’S West, Inc.
Bentonville, AR 72716
*NICODERM is a licensed trademark of the GlaxoSmithKline group of companies.
SATISFACTION GUARANTEED BY REFUND OR EXCHANGE
Made in Switzerland
Send comments/questions to:
GCSP 5.4376.4C
Consumer Relations
P.O. Box 13398
Research Triangle Park, NC 27709-9627

Principal Display Panel

NDC 68196-194-03

nicotine patch

Nicotine Transdermal System 21mg delivered over 24 hours Stop smoking aid

21 mg

SIMPLY RIGHT™

Health Care

Compare to NicoDerm®CQ®*

Includes behavior support program enrollment form & user’s guide

If you smoke more than 10 cigarettes per day: start with step 1

If you smoke 10 or less cigarettes per day: start with step 2

step 1

21 clear patches

©2011

101775XA